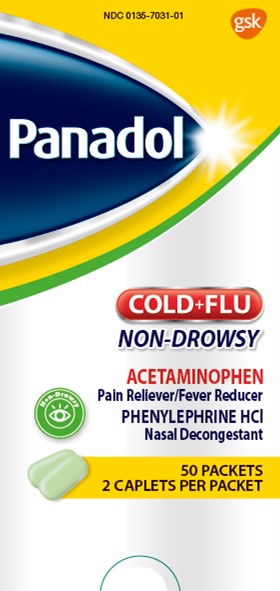 DRUG LABEL: Panadol
NDC: 0135-7031 | Form: TABLET, FILM COATED
Manufacturer: Haleon US Holdings LLC
Category: otc | Type: HUMAN OTC DRUG LABEL
Date: 20240708

ACTIVE INGREDIENTS: ACETAMINOPHEN 325 mg/1 1; PHENYLEPHRINE HYDROCHLORIDE 5 mg/1 1
INACTIVE INGREDIENTS: CROSPOVIDONE (120 .MU.M); D&C YELLOW NO. 10; FD&C BLUE NO. 1; FD&C RED NO. 40; MAGNESIUM STEARATE; MICROCRYSTALLINE CELLULOSE; POLYETHYLENE GLYCOL, UNSPECIFIED; POLYVINYL ALCOHOL, UNSPECIFIED; POVIDONE, UNSPECIFIED; STARCH, CORN; STEARIC ACID; SUCRALOSE; TALC; TITANIUM DIOXIDE

Drug Facts

Active ingredients (in each caplet)

Acetaminophen 325 mg

Phenylephrine HCl 5 mg

Purposes

Pain reliever/Fever reducer

Nasal decongestant

Uses

- temporarily relieves these symptoms due to the common cold or flu:
  - nasal congestion
  - stuffy nose
  - sore throat
  - headache
  - sinus congestion and pressure
  - minor aches and pains
- temporarily reduces fever

Warnings

Liver warning:This product contains acetaminophen. Severe liver damage may occur if you take

- more than 4,000 mg of acetaminophen in 24 hours, which is the maximum daily amount
- with other drugs containing acetaminophen
- 3 or more alcoholic drinks every day while using this product

Allergy alert:Acetaminophen may cause severe skin reactions.

Symptoms may include:

- skin reddening
- blisters
- rash

If a skin reaction occurs, stop use and seek medical help right away.

Sore throat warning:If sore throat is severe, persists for more than 2 days, is accompanied or followed by fever, headache, rash, nausea or vomiting, ask a doctor promptly.

Do not use

- with any other drug containing acetaminophen (prescription or nonprescription). If you are not sure whether a drug contains acetaminophen, ask a doctor or pharmacist.
- if you are now taking a prescription monoamine oxidase inhibitor (MAOI) (certain drugs for depression, psychiatric, or emotional conditions, or Parkinson’s disease), or for 2 weeks after stopping the MAOI drug. If you do not know if your prescription drug contains an MAOI, ask a doctor or pharmacist before taking this product.
- if you are allergic to acetaminophen or any of the inactive ingredients in this product

Ask a doctor before use if you have

- liver disease
- diabetes
- heart disease
- high blood pressure
- thyroid disease
- trouble urinating due to an enlarged prostate gland

Ask a doctor or pharmacist before use if you are

taking the blood thinning drug warfarin

Stop use and ask a doctor if

- you get nervous, dizzy or sleepless
- pain or nasal congestion gets worse or lasts more than 7 days
- fever gets worse or lasts more than 3 days
- redness or swelling is present
- any new symptoms appear

These could be signs of a serious condition.

If pregnant or breast-feeding,

ask a health professional before use.

Overdose warning:

Taking more than the recommended dose can cause serious health problems. In case of overdose, get medical help or contact a Poison Control Center right away. Quick medical attention is critical for adults as well as for children even if you do not notice any signs or symptoms.

Directions

- do not take more than directed(see overdose warning)
- adults and children 12 years of age and over: take 2 caplets every 4 hours, while symptoms persist or as directed by a doctor
- do not take more than 12 caplets in 24 hours, unless directed by a doctor
- children under 12 years of age: ask a doctor
- swallow whole – do not crush, chew or dissolve

Other information

- store below 25°C (77°F)

Inactive ingredients

crospovidone, D&C yellow no. 10 aluminum lake, FD&C blue no. 1 aluminum lake, FD&C red no. 40 aluminum lake, flavor, magnesium stearate, microcrystalline cellulose, polyethylene glycol, polyvinyl alcohol, povidone, pregelatinized starch, silicon dioxide, sodium starch glycolate, stearic acid, sucralose, talc, titanium dioxide

Principal Display Panel

NDC 0135-7031-01

Panadol

COLD+FLU

NON-DROWSY

ACETAMINOPHEN

Pain Reliever/Fever Reducer

PHENYLEPHRINE HCl

Nasal Decongestant

50 PACKETS

2 CAPLETS PER PACKET

TAMPER-EVIDENT FEATURE: This product is protected in a sealed blister. Do not use if blister or printed foil is broken.

READ AND KEEP CARTON FOR COMPLETE INFORMATION

Trademarks are owned by or licensed to the GSK group of companies.

Distributed by:

GSK Consumer Healthcare

Warren, NJ 07059

©2022 GSK group of companies or its licensor.

000079491 Front Carton